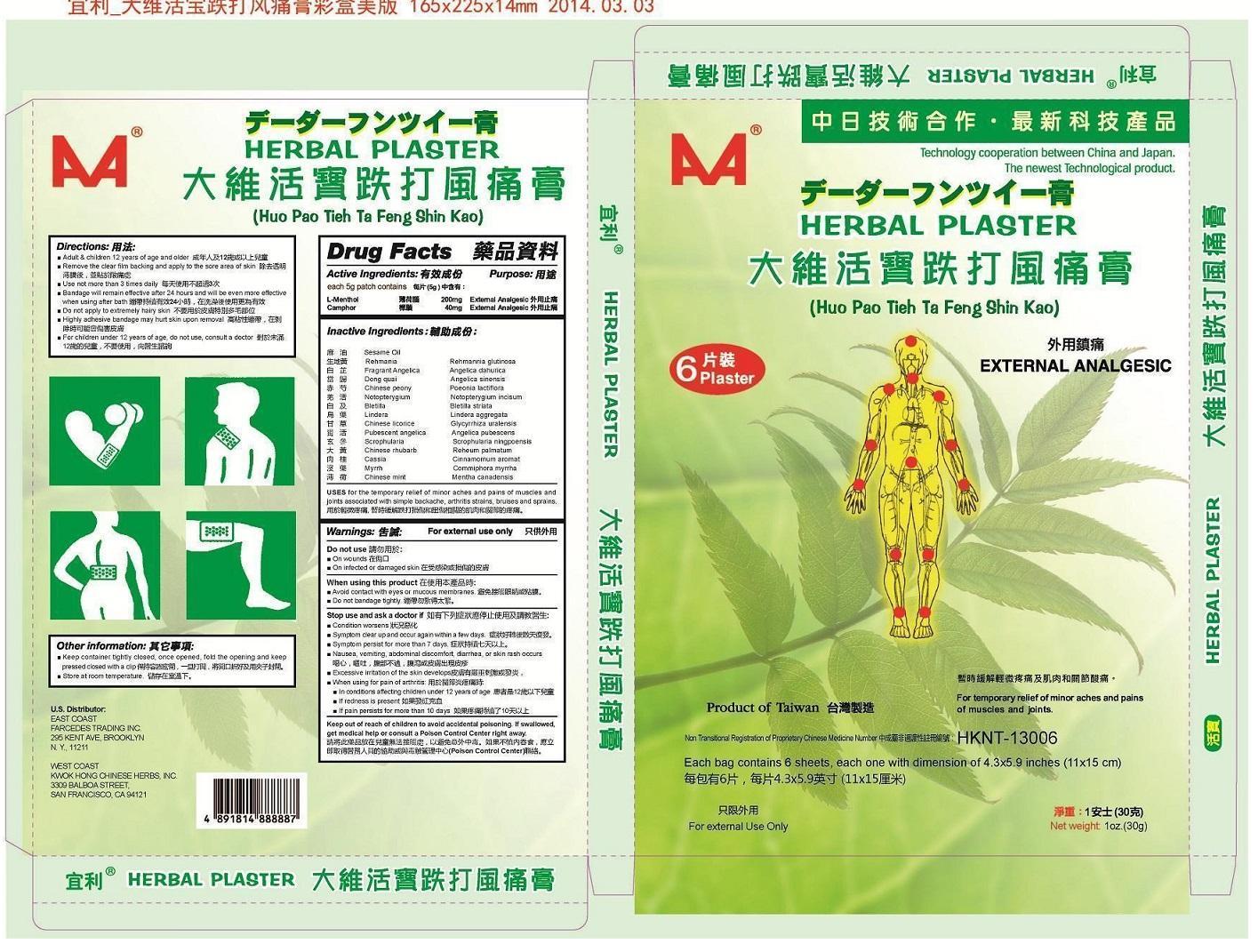 DRUG LABEL: Huo Pao Tieh Ta Feng Shin Kao
NDC: 62209-9266 | Form: PLASTER
Manufacturer: Dah Wei Biochemical Pharmaceutic International Ltd.
Category: otc | Type: HUMAN OTC DRUG LABEL
Date: 20140227

ACTIVE INGREDIENTS: LEVOMENTHOL 200 mg/5 g; CAMPHOR (SYNTHETIC) 40 mg/5 g
INACTIVE INGREDIENTS: SESAME OIL; MYRRH; REHMANNIA GLUTINOSA WHOLE; ANGELICA DAHURICA WHOLE; ANGELICA SINENSIS WHOLE; PAEONIA LACTIFLORA WHOLE; NOTOPTERYGIUM INCISUM WHOLE; BLETILLA STRIATA WHOLE; LINDERA AGGREGATA WHOLE; GLYCYRRHIZA URALENSIS; ANGELICA PUBESCENS WHOLE; SCROPHULARIA NINGPOENSIS WHOLE; RHEUM PALMATUM WHOLE; CINNAMOMUM AROMATICUM WHOLE; MENTHA ARVENSIS WHOLE

Huo Pao Tieh Ta Feng Shin Kao

Active Ingredients:

each 5 g patch contains

L-Menthol 200 mg

Camphor 40 mg

Purpose:

External analgesic

KEEP OUT OF REACH OF CHILDREN

Keep out reach of children to avoid accidental poisoning. If swallowed, get medical help or consult a poison control center right away.

Uses:

for the temporary relief of minor aches and pains of muscles and joints associated with simple backache, arthritis strains, bruises and sprains.

Warnings:

For external use only

Do not use:
■ On wounds
■ On infected or damaged skin

When using this product:

■ Avoid contact with eyes or mucous membranes.
■ Do not bandage tightly.

Stop use and ask a doctor if:

■ Condition worsens
■ Symptom clear up and occur again within a few days.
■ Symptom persist for more than 7 days.
■ Nausea, vomiting, abdominal discomfort, diarrhea, or skin rash occurs
■ Excessive irritation of the skin develops

■ When using for pain of arthritis:
■ In conditions affecting children under 12 years of age
■ If redness is present
■ If pain persists for more than 10 days

Dirctions:

- Adult & children 12 years of age and older
- Remove the clear film backing and apply to the sore area of skin.
- Use not more than three times daily
- Bandage will remain effective after 24 hours and will be even more effective when using after bath.
- Do not apply to extremely hairy skin
- Highly adhesive bandage may hurt skin upon removal
- For children under 12 years of age, do not use, consult a doctor

Other information:

- Keep container tightly closed, once opened, fold the opening and keep pressed closed with a clip
- Store at room temperature

Inactive Ingredients:

Sesame Oil

Rehmania Rehmannia glutinosa

Fragrant Angelica Angelica dahurica

Dong quai Angelica sinensis

Chinese peony Poeonia lactiflora

Notopterygium Notopterygium incisum

Bletilla Bletilla striata

Lindera Lindera aggregata

Chinese licorice Glycyrrhiza uralensis

Pubescent angelica Angelica pubescens

Scrophularia Scrophularia ningpoensis

Chinese rhubarb Reheum palmatum

Cassia Cinnamomum aromaticum

Myrrha Commiphora myrrha

Chinese mint Mentha canadensis

U.S. Distributer:

EAST COAST
FARCEDES TRADING INC.
295 KENT AVE, BROOKLYN
N,Y.,11211

WEST COAST
KWOK HONG CHINESE HERBS, INC
3309 BALBOA STREET,
SAN FRANCISCO,CA 94121